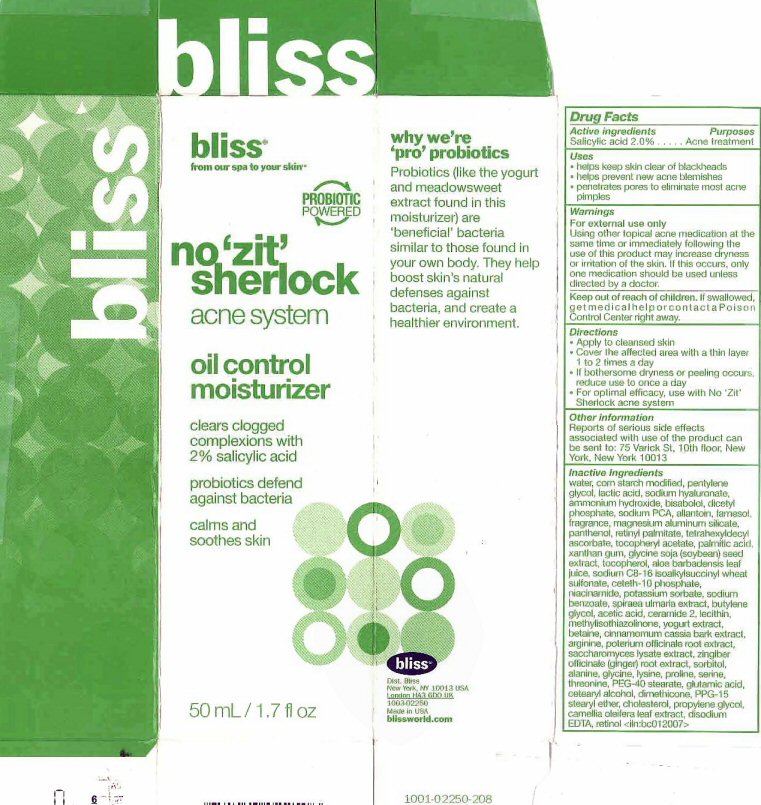 DRUG LABEL: no zit sherlock acne
NDC: 67038-107 | Form: CREAM
Manufacturer: Bliss World LLC
Category: otc | Type: HUMAN OTC DRUG LABEL
Date: 20120604

ACTIVE INGREDIENTS: SALICYLIC ACID 2 mL/100 mL
INACTIVE INGREDIENTS: WATER; STARCH, CORN; PENTYLENE GLYCOL; LACTIC ACID; HYALURONATE SODIUM; AMMONIA; LEVOMENOL; DIHEXADECYL PHOSPHATE; SODIUM PYRROLIDONE CARBOXYLATE; ALLANTOIN; FARNESOL; MAGNESIUM ALUMINUM SILICATE; PANTHENOL; VITAMIN A PALMITATE; TETRAHEXYLDECYL ASCORBATE; .ALPHA.-TOCOPHEROL ACETATE; PALMITIC ACID; XANTHAN GUM; SOYBEAN; TOCOPHEROL; ALOE VERA LEAF; CETETH-10 PHOSPHATE; NIACINAMIDE; POTASSIUM SORBATE; SODIUM BENZOATE; FILIPENDULA ULMARIA WHOLE; BUTYLENE GLYCOL ; ACETIC ACID; CERAMIDE 2; LECITHIN, SOYBEAN; METHYLISOTHIAZOLINONE; BETAINE; CHINESE CINNAMON; ARGININE; SANGUISORBA OFFICINALIS ROOT; SACCHAROMYCES LYSATE; GINGER; SORBITOL; ALANINE; GLYCINE; LYSINE; PROLINE; SERINE; THREONINE; PEG-40 STEARATE; GLUTAMIC ACID; CETOSTEARYL ALCOHOL; DIMETHICONE; PPG-15 STEARYL ETHER; CHOLESTEROL; PROPYLENE GLYCOL; CAMELLIA OLEIFERA LEAF; EDETATE DISODIUM; RETINOL

Active Ingredients

Drug Facts

Active ingredients

Salicylic acid 2.0%

Purposes

Acne treatment

Keep out of reach of children. If swallowed, get medical help or contact a Poison Control Center right away.

Uses

- helps keep skin clear of blackheads
- helps prevent new acne blemishes
- penetrates pores to eliminate most acne pimples

Warnings

For external use only

Using other topical acne medication at the same time or immediately following the use of this product may increase dryness or irritation of the skin. If this occurs, only one medication should be used unless directed by a doctor.

Directions

- Apply to cleansed skin
- Cover the affected area with a thin layer 1 to 2 times a day
- If bothersome dryness or peeling occurs, reduce use to once a day
- For optimal efficacy, use with No 'Zit' Sherlock acne system

Other information

Reports on serious side effects associated with the use of the product can be sent to: 75 Varick St. 10th Floor, New York, New York 10013

Inactive Ingredients

water, corn starch modified, pentylene glycol, lactic acid, sodium hyaluronate, ammonium hydroxide,, bisabolol, dicetly phosphate, sodium PCA, allantoin, farnesol, fragrance, magnesium aluminum silicate, panthenol, retinyl palmitate, tetrahexyldecyl ascorbate, tocopheryl acetate, palmitic acid, xanthan gum, glycine soja (soybean) seed extract, tocopherol, aloe barbadensis leaf juice, sodium C8-16 isoalkylsuccinyl wheat sulfonate, ceteth-10 phosphate, niacinamide, potassium sorbate,sodium benzoate, spiraea ulmaria extract, butylene glycol, acetic acid, ceramide 2, lecithin, methylisothialinone, yogurt extract, bentane, cinnamomum cassia bark extract, arginine, poterium officinale root extract, saccharomyces lysate extract, zingiber officinale (ginger) root extract, sorbitol, alanine, glycine, lysine, proline, serine, threonine, PEG-40 stearate, glutamic acid, cetearyl alcohol, dimethicone, PPG-15 stearyl ether, cholesterol, propylene glycol, camellia oleifera leaf extract, disodium EDTA, retinol

Package Label

bliss from our spa to your skin PROBIOTIC POWERED

no 'zit' sherlock acne system oil control moisturizer

clears clogged complexions with 2% salicylic acid probiotics defend against bacteria calms and soothes skin

why we're 'pro' probiotics Probiotics (like the yogurt and meadowsweet extract found in this moisturizer) are 'beneficial' bacteria similar to those found in your own body. They help boost skin's natural defenses against bacteria and create a healthier environment.

bliss dist Bliss New York NY 10013 USA London HA3 6DO UK 1003-02250 Made in USA blissworld.com

50mL/1.7 fl oz 1001-02250-208